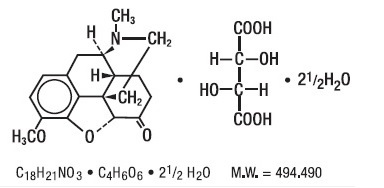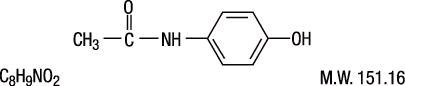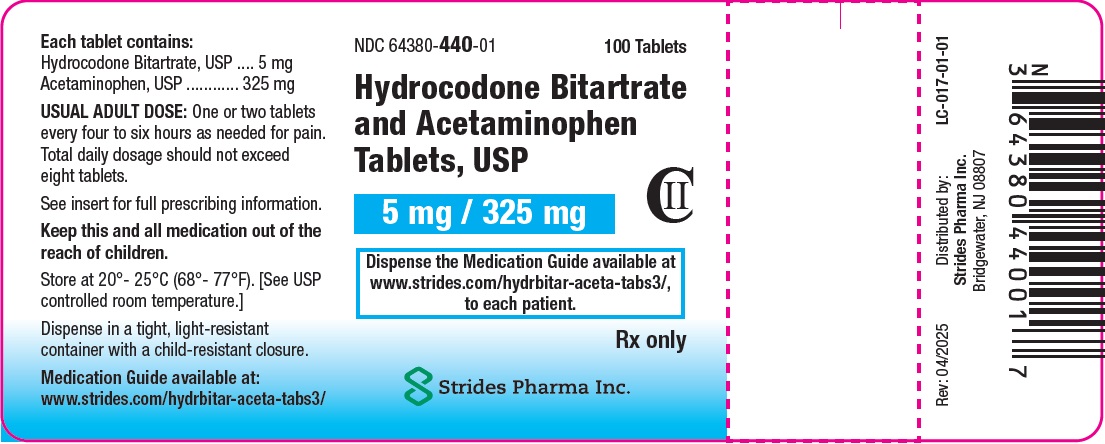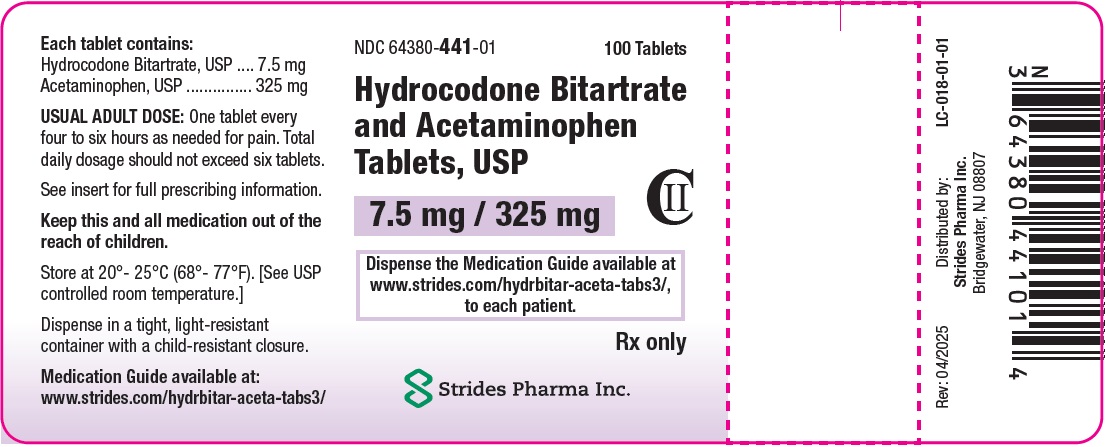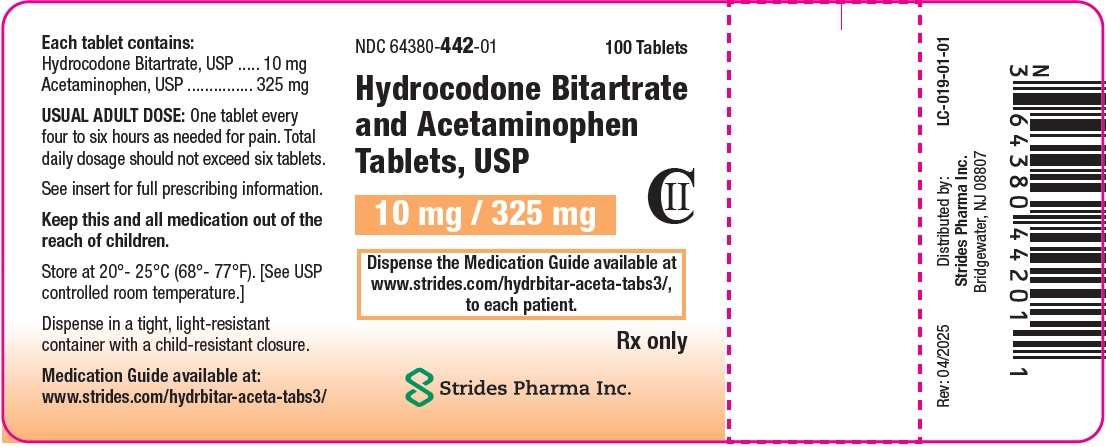 DRUG LABEL: hydrocodone bitartrate and acetaminophen
NDC: 64380-440 | Form: TABLET
Manufacturer: Strides Pharma Science Limited
Category: prescription | Type: HUMAN PRESCRIPTION DRUG LABEL
Date: 20260223
DEA Schedule: CII

ACTIVE INGREDIENTS: HYDROCODONE BITARTRATE 5 mg/1 1; ACETAMINOPHEN 325 mg/1 1
INACTIVE INGREDIENTS: SILICON DIOXIDE; CROSPOVIDONE; MAGNESIUM STEARATE; MICROCRYSTALLINE CELLULOSE; POVIDONE; STARCH, CORN; STEARIC ACID

Hydrocodone Bitartrate and Acetaminophen Tablets USP

BOXED WARNING

WARNING: SERIOUS AND LIFE-THREATENING RISKS FROM USE OF HYDROCODONE BITARTRATE AND ACETAMINOPHEN TABLETS

Addiction, Abuse, and Misuse

Because the use of Hydrocodone Bitartrate and Acetaminophen tablets expose patients and other users to the risks of opioid addiction, abuse, and misuse, which can lead to overdose and death, assess each patient's risk prior to prescribing and reassess all patients regularly for the development of these behaviors and conditions [see Warnings].

Life-Threatening Respiratory Depression

Serious, life-threatening, or fatal respiratory depression may occur with use of Hydrocodone Bitartrate and Acetaminophen tablets, especially during initiation or following a dosage increase. To reduce the risk of respiratory depression, proper dosing and titration of Hydrocodone Bitartrate and Acetaminophen tablets are essential [see Warnings].

Accidental Ingestion

Accidental ingestion of even one dose of Hydrocodone Bitartrate and Acetaminophen tablets, especially by children, can result in a fatal overdose of Hydrocodone [see Warnings].

Risks From Concomitant Use with Benzodiazepines or Other CNS Depressants

Concomitant use of opioids with benzodiazepines or other central nervous system (CNS) depressants, including alcohol, may result in profound sedation, respiratory depression, coma, and death. Reserve concomitant prescribing of Hydrocodone Bitartrate and Acetaminophen tablets and benzodiazepines or other CNS depressants for use in patients for whom alternative treatment options are inadequate [see Warnings, Precautions; Drug Interactions].

Neonatal Opioid Withdrawal Syndrome (NOWS)

Advise pregnant women using opioids for an extended period of time of the risk of Neonatal Opioid Withdrawal Syndrome, which may be life-threatening if not recognized and treated. Ensure that management by neonatology experts will be available at delivery [see Warnings].

Opioid Analgesic Risk Evaluation and Mitigation Strategy (REMS)

Healthcare providers are strongly encouraged to complete a REMS-compliant education program and to counsel patients and caregivers on serious risks, safe use, and the importance of reading the Medication Guide with each prescription [see Warnings].

Cytochrome P450 3A4 Interaction

The concomitant use of Hydrocodone Bitartrate and Acetaminophen Tablets with all Cytochrome P450 3A4 inhibitors may result in an increase in hydrocodone plasma concentrations, which could increase or prolong adverse reactions and may cause potentially fatal respiratory depression. In addition, discontinuation of a concomitantly used Cytochrome P450 3A4 inducer may result in an increase in hydrocodone plasma concentrations. Monitor patients receiving Hydrocodone Bitartrate and Acetaminophen Tablets and any Cytochrome P450 3A4 inhibitor or inducer for signs of respiratory depression or sedation [see Clinical Pharmacology, Warnings, Precautions; Drug Interactions].

Hepatotoxicity

Acetaminophen has been associated with cases of acute liver failure, at times resulting in liver transplant and death. Most of the cases of liver injury are associated with the use of acetaminophen at doses that exceed 4,000 milligrams per day, and often involve more than one acetaminophen-containing product [see Warnings, Overdosage].

DESCRIPTION

Hydrocodone Bitartrate and Acetaminophen Tablets, USP is supplied in tablet form for oral administration.

Hydrocodone bitartrate is an opioid analgesic and antitussive and occurs as fine, white crystals or as a crystalline powder. It is affected by light. The chemical name is 4,5 α -Epoxy-3-methoxy-17-methylmorphinan-6-one tartrate (1:1) hydrate (2:5). It has the following structural formula:

Acetaminophen, 4´-Hydroxyacetanilide, a slightly bitter, white, odorless, crystalline powder, is a non-opiate, non-salicylate analgesic and antipyretic. It has the following structural formula:

Each Hydrocodone Bitartrate and Acetaminophen Tablet, 5 mg/325 mg contains:

Hydrocodone Bitartrate …..... 5 mg

Acetaminophen ................. 325 mg

Each Hydrocodone Bitartrate and Acetaminophen Tablet, 7.5 mg/325 mg contains:

Hydrocodone Bitartrate ......... 7.5 mg

Acetaminophen ..................... 325 mg

Each Hydrocodone Bitartrate and Acetaminophen Tablets, 10 mg/325 mg contains:

Hydrocodone Bitartrate .......... 10 mg

Acetaminophen ..................... 325 mg

In addition, each tablet contains the following inactive ingredients: colloidal silicon dioxide, crospovidone, magnesium stearate, microcrystalline cellulose, povidone, pregelatinized starch, and stearic acid. Meets USP Dissolution Test 1.

CLINICAL PHARMACOLOGY

Mechanism of Action

Hydrocodone is full opioid agonist with relative selectivity for the mu-opioid (µ) receptor, although it can interact with other opioid receptors at higher doses. The principal therapeutic action of hydrocodone is analgesia. Like all full opioid agonists, there is no ceiling effect for analgesia with hydrocodone. Clinically, dosage is titrated to provide adequate analgesia and may be limited by adverse reactions, including respiratory and CNS depression.

The precise mechanism of the analgesic action is unknown. However, specific CNS opioid receptors for endogenous compounds with opioid-like activity have been identified throughout the brain and spinal cord and are thought to play a role in the analgesic effects of this drug.

The precise mechanism of the analgesic properties of acetaminophen is not established but is thought to involve central actions.

Pharmacodynamics

Effects on the Central Nervous System

The principal therapeutic action of hydrocodone is analgesia. Hydrocodone produces respiratory depression by direct action on brain stem respiratory centers. The respiratory depression involves a reduction in the responsiveness of the brain stem respiratory centers to both increases in carbon dioxide tension and electrical stimulation.

Hydrocodone causes miosis, even in total darkness. Pinpoint pupils are a sign of opioid overdose but are not pathognomonic (e.g., pontine lesions of hemorrhagic or ischemic origins may produce similar findings). Marked mydriasis rather than miosis may be seen due to hypoxia in overdose situations.

Therapeutic doses of acetaminophen have negligible effects on the cardiovascular or respiratory systems; however, toxic doses may cause circulatory failure and rapid, shallow breathing.

Effects on the Gastrointestinal Tract and Other Smooth Muscle

Hydrocodone causes a reduction in motility associated with an increase in smooth muscle tone in the antrum of the stomach and duodenum. Digestion of food in the small intestine is delayed and propulsive contractions are decreased. Propulsive peristaltic waves in the colon are decreased, while tone may be increased to the point of spasm, resulting in constipation. Other opioid-induced effects may include a reduction in biliary and pancreatic secretions, spasm of sphincter of Oddi, transient elevations in serum amylase, and opioid-induced esophageal dysfunction (OIED).

Effects on the Cardiovascular System

Hydrocodone produces peripheral vasodilation which may result in orthostatic hypotension or syncope. Manifestations of histamine release and/or peripheral vasodilation may include pruritus, flushing, red eyes, sweating, and/or orthostatic hypotension.

Effects on the Endocrine System

Opioids inhibit the secretion of adrenocorticotropic hormone (ACTH), cortisol, and luteinizing hormone (LH) in humans [see Adverse Reactions]. They also stimulate prolactin, growth hormone (GH) secretion, and pancreatic secretion of insulin and glucagon.

Use of opioids for an extended period of time may influence the hypothalamic-pituitary-gonadal axis, leading to androgen deficiency that may manifest as symptoms as low libido, impotence, erectile dysfunction, amenorrhea, or infertility. The causal role of opioids in the syndrome of hypogonadism is unknown because the various medical, physical, lifestyle, and psychological stressors that may influence gonadal hormone levels have not been adequately controlled for in studies conducted to date [see Adverse Reactions].

Effects on the Immune System

Opioids have been shown to have a variety of effects on components of the immune system. The clinical significance of these findings is unknown. Overall, the effects of opioids appear to be modestly immunosuppressive.

Concentration–Efficacy Relationships

The minimum effective analgesic concentration will vary widely among patients, especially among patients who have been previously treated with opioid agonists. The minimum effective analgesic concentration of hydrocodone for any individual patient may increase over time due to an increase in pain, the development of a new pain syndrome, and/or the development of analgesic tolerance [see Dosage and Administration].

Concentration–Adverse Reaction Relationships

There is a relationship between increasing hydrocodone plasma concentration and increasing frequency of dose-related opioid adverse reactions such as nausea, vomiting, CNS effects, and respiratory depression. In opioid-tolerant patients, the situation may be altered by the development of tolerance to opioid-related adverse reactions [see Dosage and Administration].

Pharmacokinetics

The behavior of the individual components is described below.

Hydrocodone

Following a 10 mg oral dose of hydrocodone administered to five adult male subjects, the mean peak concentration was 23.6 ± 5.2 ng/mL. Maximum serum levels were achieved at 1.3 ± 0.3 hours and the half-life was determined to be 3.8 ± 0.3 hours.

Hydrocodone exhibits a complex pattern of metabolism including O-demethylation, N-demethylation and 6-keto reduction to the corresponding 6-α- and 6-β-hydroxymetabolites. See OVERDOSAGE for toxicity information.

CYP3A4 mediated N-demethylation to norhydrocodone is the primary metabolic pathway of hydrocodone with a lower contribution from CYP2D6 mediated O-demethylation to hydromorphone. Hydromorphone is formed from the O-demethylation of hydrocodone and may contribute to the total analgesic effect of hydrocodone. Therefore, the formation of these and related metabolites can, in theory, be affected by other drugs [see Precautions; Drug Interactions]. N-demethylation of hydrocodone to form norhydrocodone via CYP3A4 while O-demethylation of hydrocodone to hydromorphone is predominantly catalyzed by CYP2D6 and to a lesser extent by an unknown low affinity CYP enzyme. Hydrocodone and its metabolites are eliminated primarily in the kidneys.

Acetaminophen

Acetaminophen is rapidly absorbed from the gastrointestinal tract and is distributed throughout most body tissues. A small fraction (10-25%) of acetaminophen is bound to plasma proteins. The plasma half- life is 1.25 to 3 hours, but may be increased by liver damage and following overdosage. Elimination of acetaminophen is principally by liver metabolism (conjugation) and subsequent renal excretion of metabolites. Acetaminophen is primarily metabolized in the liver by first-order kinetics and involves three principal separate pathways: conjugation with glucuronide; conjugation with sulfate; and oxidation via the cytochrome, P450-dependent, mixed-function oxidase enzyme pathway to form a reactive intermediate metabolite, which conjugates with glutathione and is then further metabolized to form cysteine and mercapturic acid conjugates. The principal cytochrome P450 isoenzyme involved appears to be CYP2E1, with CYP1A2 and CYP3A4 as additional pathways. Approximately 85% of an oral dose appears in the urine within 24 hours of administration, most as the glucuronide conjugate, with small amounts of other conjugates and unchanged drug.

See OVERDOSAGE for toxicity information.

INDICATIONS AND USAGE

Hydrocodone bitartrate and acetaminophen tablets are indicated for the management of pain severe enough to require an opioid analgesic and for which alternative treatments are inadequate.

Limitations of Use:

Because of the risks of addiction, abuse, misuse, overdose, and death, which can occur at any dosage or duration and persist over the course of therapy [see WARNINGS], reserve opioid analgesics, including Hydrocodone Bitartrate and Acetaminophen Tablets, for use in patients for whom alternative treatment options are ineffective, not tolerated, or would be otherwise inadequate to provide sufficient management of pain.

CONTRAINDICATIONS

Hydrocodone Bitartrate and Acetaminophen Tablets are contraindicated in patients with:

- Significant respiratory depression [see Warnings]
- Acute or severe bronchial asthma in an unmonitored setting or in the absence of resuscitative equipment [see Warnings]
- Known or suspected gastrointestinal obstruction, including paralytic ileus [see Warnings]
- Hypersensitivity to hydrocodone or acetaminophen (e.g., anaphylaxis) [see Warnings, Adverse Reactions]

WARNINGS

Addiction, Abuse, and Misuse

Hydrocodone Bitartrate and Acetaminophen Tablets contain hydrocodone, a Schedule II controlled substance. As an opioid, Hydrocodone Bitartrate and Acetaminophen Tablets exposes users to the risks of addiction, abuse, and misuse [see Drug Abuse and Dependence].

Although the risk of addiction in any individual is unknown, it can occur in patients appropriately prescribed Hydrocodone Bitartrate and Acetaminophen Tablets. Addiction can occur at recommended dosages and if the drug is misused or abused. The risk of opioid-related overdose or overdose-related death is increased with higher opioid doses, and this risk persists over the course of therapy. In postmarketing studies, addiction, abuse, misuse, and fatal and non-fatal opioid overdose were observed in patients with long-term opioid use [see ADVERSE REACTIONS].

Assess each patient's risk for opioid addiction, abuse, or misuse prior to prescribing Hydrocodone Bitartrate and Acetaminophen Tablets, and reassess all patients receiving Hydrocodone Bitartrate and Acetaminophen Tablets for the development of these behaviors and conditions. Risks are increased in patients with a personal or family history of substance abuse (including drug or alcohol abuse or addiction) or mental illness (e.g., major depression). The potential for these risks should not, however, prevent the proper management of pain in any given patient. Patients at increased risk may be prescribed opioids such as Hydrocodone Bitartrate and Acetaminophen Tablets, but use in such patients necessitates intensive counseling about the risks and proper use of Hydrocodone Bitartrate and Acetaminophen Tablets along with frequent reevaluation for signs of addiction, abuse, and misuse. Consider recommending or prescribing an opioid overdose reversal agent [see WARNINGS, DOSAGE AND ADMINISTRATION].

Opioids are sought for nonmedical use and are subject to diversion from legitimate prescribed use. Consider these risks when prescribing or dispensing Hydrocodone Bitartrate and Acetaminophen Tablets. Strategies to reduce these risks include prescribing the drug in the smallest appropriate quantity and advising the patient on careful storage of the drug during the course of treatment and proper disposal of unused drug. Contact local state professional licensing board or state-controlled substances authority for information on how to prevent and detect abuse or diversion of this product.

Life-Threatening Respiratory Depression

Serious, life-threatening, or fatal respiratory depression has been reported with the use of opioids, even when used as recommended. Respiratory depression, if not immediately recognized and treated, may lead to respiratory arrest and death. Management of respiratory depression may include close observation, supportive measures, and use of opioid overdose reversal agents, depending on the patient's clinical status [see Overdosage]. Carbon dioxide (CO2) retention from opioid-induced respiratory depression can exacerbate the sedating effects of opioids.

While serious, life-threatening, or fatal respiratory depression can occur at any time during the use of Hydrocodone Bitartrate and Acetaminophen Tablets, the risk is greatest during the initiation of therapy or following a dosage increase.

To reduce the risk of respiratory depression, proper dosing and titration of Hydrocodone Bitartrate and Acetaminophen Tablets are essential [see Dosage and Administration]. Overestimating the Hydrocodone Bitartrate and Acetaminophen Tablets dosage when converting patients from another opioid product can result in a fatal overdose.

Accidental ingestion of even one dose of Hydrocodone Bitartrate and Acetaminophen Tablets, especially by children, can result in respiratory depression and death due to an overdose of Hydrocodone Bitartrate and Acetaminophen Tablets.

Educate patients and caregivers on how to recognize respiratory depression and emphasize the importance of calling 911 or getting emergency medical help right away in the event of a known or suspected overdose [see Precautions, Information for Patients].

Opioids can cause sleep-related breathing disorders including central sleep apnea (CSA) and sleep-related hypoxemia. Opioid use increases the risk of CSA in a dose-dependent fashion. In patients who present with CSA, consider decreasing the opioid dosage using best practices for opioid taper [see Dosage and Administration].

Patient Access to an Opioid Overdose Reversal Agent for the Emergency Treatment of Opioid Overdose

Inform patients and caregivers about opioid overdose reversal agents (e.g., naloxone, nalmefene). Discuss the importance of having access to an opioid overdose reversal agent, especially if the patient has risk factors for overdose (e.g., concomitant use of CNS depressants, a history of opioid use disorder, or prior opioid overdose) or if there are household members (including children) or other close contacts at risk for accidental ingestion or opioid overdose. The presence of risk factors for overdose should not prevent the management of pain in any patient [see WARNINGS].

Discuss the options for obtaining an opioid overdose reversal agent (e.g., prescription, over-the-counter, or as part of a community-based program).

There are important differences among the opioid overdose reversal agents, such as route of administration, product strength, approved patient age range, and pharmacokinetics. Be familiar with these differences, as outlined in the approved labeling for those products, prior to recommending or prescribing such an agent.

Educate patients and caregivers on how to recognize respiratory depression, and how to use an opioid overdose reversal agent for the emergency treatment of opioid overdose. Emphasize the importance of calling 911 or getting emergency medical help, even if an opioid overdose reversal agent is administered [see WARNINGS, OVERDOSAGE].

Risks from Concomitant Use with Benzodiazepines or Other CNS Depressants

Profound sedation, respiratory depression, coma, and death may result from the concomitant use of

Hydrocodone Bitartrate and Acetaminophen Tablets with benzodiazepines and/or other CNS depressants, including alcohol (e.g., non-benzodiazepine sedatives/hypnotics, anxiolytics, tranquilizers, muscle relaxants, general anesthetics, antipsychotics, gabapentinoids [gabapentin or pregabalin], and other opioids). Because of these risks, reserve concomitant prescribing of these drugs for use in patients for whom alternative treatment options are inadequate.

Observational studies have demonstrated that concomitant use of opioid analgesics and benzodiazepines increases the risk of drug-related mortality compared to use of opioid analgesics alone. Because of similar pharmacological properties, it is reasonable to expect similar risk with the concomitant use of other CNS depressant drugs with opioid analgesics [see Precautions; Drug Interactions].

If the decision is made to prescribe a benzodiazepine or other CNS depressant concomitantly with an opioid analgesic, prescribe the lowest effective dosages and minimum durations of concomitant use. In patients already receiving an opioid analgesic, prescribe a lower initial dose of the benzodiazepine or other CNS depressant than indicated in the absence of an opioid, and titrate based on clinical response. If an opioid analgesic is initiated in a patient already taking a benzodiazepine or other CNS depressant, prescribe a lower initial dose of the opioid analgesic, and titrate based on clinical response. Inform patients and caregivers of this potential interaction and educate them on the signs and symptoms of respiratory depression (including sedation).

If concomitant use is warranted, consider recommending or prescribing an opioid overdose reversal agent [see WARNINGS, DOSAGE AND ADMINISTRATION].

Advise both patients and caregivers about the risks of respiratory depression and sedation when Hydrocodone Bitartrate and Acetaminophen Tablets are used with benzodiazepines or other CNS depressants (including alcohol and illicit drugs). Advise patients not to drive or operate heavy machinery until the effects of concomitant use of the benzodiazepine or other CNS depressant have been determined. Screen patients for risk of substance use disorders, including opioid abuse and misuse, and warn them of the risk for overdose and death associated with the use of additional CNS depressants including alcohol and illicit drugs [see Precautions: Drug Interactions, Information for Patients].

Neonatal Opioid Withdrawal Syndrome

Use of Hydrocodone Bitartrate and Acetaminophen Tablets for an extended period of time during pregnancy can result in withdrawal in the neonate. Neonatal opioid withdrawal syndrome, unlike opioid withdrawal syndrome in adults, may be life-threatening if not recognized and treated, and requires management according to protocols developed by neonatology experts. Observe newborns for signs of neonatal opioid withdrawal syndrome and manage accordingly. Advise pregnant women using opioids for an extended period of time of the risk of neonatal opioid withdrawal syndrome and ensure that appropriate treatment will be available [see Precautions; Information for Patients, Pregnancy].

Opioid Analgesic Risk Evaluation and Mitigation Strategy (REMS)

To ensure that the benefits of opioid analgesics outweigh the risks of addiction, abuse, and misuse, the Food and Drug Administration (FDA) has required a Risk Evaluation and Mitigation Strategy (REMS) for these products. Under the requirements of the REMS, drug companies with approved opioid analgesic products must make REMS-compliant education programs available to healthcare providers. Healthcare providers are strongly encouraged to do all of the following:

- Complete a REMS-compliant education program offered by an accredited provider of continuing education (CE) or another education program that includes all the elements of the FDA Education Blueprint for Health Care Providers Involved in the Management or Support of Patients with Pain.
- Discuss the safe use, serious risks, and proper storage and disposal of opioid analgesics with patients and/or their caregivers every time these medicines are prescribed. The Patient Counseling Guide (PCG) can be obtained at this link: www.fda.gov/OpioidAnalgesicREMSPCG.
- Emphasize to patients and their caregivers the importance of reading the Medication Guide that they will receive from their pharmacist every time an opioid analgesic is dispensed to them.
- Consider using other tools to improve patient, household, and community safety, such as patient-prescriber agreements that reinforce patient-prescriber responsibilities.

To obtain further information on the opioid analgesic REMS and for a list of accredited REMS CME/CE, call 800-503-0784, or log on to www.opioidanalgesicrems.com. The FDA Blueprint can be found at www.fda.gov/OpioidAnalgesicREMSBlueprint.

Risks of Concomitant Use or Discontinuation of Cytochrome P450 3A4 Inhibitors and Inducers

Concomitant use of Hydrocodone Bitartrate and Acetaminophen Tablets with a CYP3A4 inhibitor, such as macrolide antibiotics (e.g., erythromycin), azole-antifungal agents (e.g., ketoconazole), and protease inhibitors (e.g., ritonavir), may increase plasma concentrations of Hydrocodone Bitartrate and Acetaminophen Tablets and prolong opioid adverse reactions, and which may cause potentially fatal respiratory depression [see Warnings], particularly when an inhibitor is added after a stable dose of Hydrocodone Bitartrate and Acetaminophen Tablets is achieved. Similarly, discontinuation of a CYP3A4 inducer, such as rifampin, carbamazepine, and phenytoin, in Hydrocodone Bitartrate and Acetaminophen Tablets-treated patients may increase hydrocodone plasma concentrations and prolong opioid adverse reactions. When adding CYP3A4 inhibitors or discontinuing CYP3A4 inducers in Hydrocodone Bitartrate and Acetaminophen Tablets-treated patients, evaluate patients at frequent intervals and consider dosage reduction of Hydrocodone Bitartrate and Acetaminophen Tablets until stable drug effects are achieved [see Precautions; Drug Interactions].

Concomitant use of Hydrocodone Bitartrate and Acetaminophen Tablets with CYP3A4 inducers or discontinuation of an CYP3A4 inhibitor could decrease hydrocodone plasma concentrations, decrease opioid efficacy or, possibly, lead to a withdrawal syndrome in a patient who had developed physical dependence to hydrocodone. When using Hydrocodone Bitartrate and Acetaminophen Tablets with CYP3A4 inducers or discontinuing CYP3A4 inhibitors, follow patients at frequent intervals and consider increasing the opioid dosage if needed to maintain adequate analgesia or if symptoms of opioid withdrawal occur [see Precautions; Drug Interactions].

Hepatotoxicity

Acetaminophen has been associated with cases of acute liver failure, at times resulting in liver transplant and death. Most of the cases of liver injury are associated with the use of acetaminophen at doses that exceed 4,000 milligrams per day, and often involve more than one acetaminophen-containing product. The excessive intake of acetaminophen may be intentional to cause self-harm or unintentional as patients attempt to obtain more pain relief or unknowingly take other acetaminophen-containing products.

The risk of acute liver failure is higher in individuals with underlying liver disease and in individuals who ingest alcohol while taking acetaminophen.

Instruct patients to look for acetaminophen or APAP on package labels and not to use more than one product that contains acetaminophen. Instruct patients to seek medical attention immediately upon ingestion of more than 4,000 milligrams of acetaminophen per day, even if they feel well.

Opioid-Induced Hyperalgesia and Allodynia

Opioid-Induced Hyperalgesia (OIH) occurs when an opioid analgesic paradoxically causes an increase in pain, or an increase in sensitivity to pain. This condition differs from tolerance, which is the need for increasing doses of opioids to maintain a defined effect [see Dependence]. Symptoms of OIH include (but may not be limited to) increased levels of pain upon opioid dosage increase, decreased levels of pain upon opioid dosage decrease, or pain from ordinarily non-painful stimuli (allodynia). These symptoms may suggest OIH only if there is no evidence of underlying disease progression, opioid tolerance, opioid withdrawal, or addictive behavior.

Cases of OIH have been reported, both with short-term and longer-term use of opioid analgesics. Though the mechanism of OIH is not fully understood, multiple biochemical pathways have been implicated. Medical literature suggests a strong biologic plausibility between opioid analgesics and OIH and allodynia. If a patient is suspected to be experiencing OIH, carefully consider appropriately decreasing the dose of the current opioid analgesic or opioid rotation (safely switching the patient to a different opioid moiety) [see Dosage and Administration, Warnings].

Life-Threatening Respiratory Depression in Patients with Chronic Pulmonary Disease or in Elderly, Cachectic, or Debilitated Patients

The use of Hydrocodone Bitartrate and Acetaminophen Tablets in patients with acute or severe bronchial asthma in an unmonitored setting or in the absence of resuscitative equipment is contraindicated.

Patients with Chronic Pulmonary Disease: Hydrocodone Bitartrate and Acetaminophen Tablet-treated patients with significant chronic obstructive pulmonary disease or cor pulmonale, and those with a substantially decreased respiratory reserve, hypoxia, hypercapnia, or pre-existing respiratory depression are at increased risk of decreased respiratory drive including apnea, even at recommended dosages of Hydrocodone Bitartrate and Acetaminophen Tablets [see Warnings; Life-Threatening Respiratory Depression].

Elderly, Cachetic, or Debilitated Patients: Life-threatening respiratory depression is more likely to occur in elderly, cachectic, or debilitated patients because they may have altered pharmacokinetics or altered clearance compared to younger, healthier patients [see Warnings; Life-Threatening Respiratory Depression].

Regularly evaluate patients, particularly when initiating and titrating Hydrocodone Bitartrate and Acetaminophen Tablets and when Hydrocodone Bitartrate and Acetaminophen Tablets is given concomitantly with other drugs that depress respiration [see Warnings]. Alternatively, consider the use of non-opioid analgesics in these patients.

Adrenal Insufficiency

Cases of adrenal insufficiency have been reported with opioid use, more often following greater than one month of use. Presentation of adrenal insufficiency may include non-specific symptoms and signs including nausea, vomiting, anorexia, fatigue, weakness, dizziness, and low blood pressure. If adrenal insufficiency is suspected, confirm the diagnosis with diagnostic testing as soon as possible. If adrenal insufficiency is diagnosed, treat with physiologic replacement doses of corticosteroids. Wean the patient off of the opioid to allow adrenal function to recover and continue corticosteroid treatment until adrenal function recovers. Other opioids may be tried as some cases reported use of a different opioid without recurrence of adrenal insufficiency. The information available does not identify any particular opioids as being more likely to be associated with adrenal insufficiency.

Severe Hypotension

Hydrocodone Bitartrate and Acetaminophen Tablets may cause severe hypotension including orthostatic hypotension and syncope in ambulatory patients. There is increased risk in patients whose ability to maintain blood pressure has already been compromised by a reduced blood volume or concurrent administration of certain CNS depressant drugs (e.g., phenothiazines or general anesthetics) [see Precautions; Drug Interactions]. Regularly evaluate these patients for signs of hypotension after initiating or titrating the dosage of Hydrocodone Bitartrate and Acetaminophen Tablets. In patients with circulatory shock Hydrocodone Bitartrate and Acetaminophen Tablets may cause vasodilatation that can further reduce cardiac output and blood pressure. Avoid the use of Hydrocodone Bitartrate and Acetaminophen Tablets with circulatory shock.

Serious Skin Reactions

Rarely, acetaminophen may cause serious skin reactions such as acute generalized exanthematous pustulosis (AGEP), Stevens-Johnson Syndrome (SJS), and toxic epidermal necrolysis (TEN), which can be fatal. Patients should be informed about the signs of serious skin reactions, and use of the drug should be discontinued at the first appearance of skin rash or any other sign of hypersensitivity.

Hypersensitivity/Anaphylaxis

There have been post-marketing reports of hypersensitivity and anaphylaxis associated with the use of acetaminophen. Clinical signs included swelling of the face, mouth, and throat, respiratory distress, urticaria, rash, pruritus, and vomiting. There were infrequent reports of life-threatening anaphylaxis requiring emergency medical attention. Instruct patients to discontinue Hydrocodone Bitartrate and Acetaminophen Tablets immediately and seek medical care if they experience these symptoms. Do not prescribe Hydrocodone Bitartrate and Acetaminophen Tablets for patients with acetaminophen allergy [see Precautions; Information for Patients/Caregivers].

Risks of Use in Patients with Increased Intracranial Pressure, Brain Tumors, Head Injury, or Impaired Consciousness

In patients who may be susceptible to the intracranial effects of CO2 retention (e.g., those with evidence of increased intracranial pressure or brain tumors), Hydrocodone Bitartrate and Acetaminophen Tablets may reduce respiratory drive, and the resultant CO2 retention can further increase intracranial pressure. Regularly evaluate patients for signs of sedation and respiratory depression, particularly when initiating therapy with Hydrocodone Bitartrate and Acetaminophen Tablets.

Opioids may also obscure the clinical course in a patient with a head injury. Avoid the use of Hydrocodone Bitartrate and Acetaminophen Tablets in patients with impaired consciousness or coma.

Risks of Gastrointestinal Complications

Hydrocodone Bitartrate and Acetaminophen Tablets are contraindicated in patients with known or suspected gastrointestinal obstruction, including paralytic ileus.

The administration of Hydrocodone Bitartrate and Acetaminophen Tablets or other opioids may obscure the diagnosis or clinical course in patients with acute abdominal conditions.

The Hydrocodone in Hydrocodone Bitartrate and Acetaminophen Tablets may cause spasm of the sphincter of Oddi. Opioids may cause increases in serum amylase. Regularly evaluate patients with biliary tract disease, including acute pancreatitis, for worsening symptoms.

Cases of opioid-induced esophageal dysfunction (OIED) have been reported in patients taking opioids. The risk of OIED may increase as the dose and/or duration of opioids increases. Regularly evaluate patients for signs and symptoms of OIED (e.g., dysphagia, regurgitation, non-cardiac chest pain), and if necessary, adjust opioid therapy as clinically appropriate [see CLINICAL PHARMACOLOGY].

Increased Risk of Seizures in Patients with Seizure Disorders

The hydrocodone in Hydrocodone Bitartrate and Acetaminophen Tablets may increase the frequency of seizures in patients with seizure disorders, and may increase the risk of seizures occurring in other clinical settings associated with seizures. Regularly evaluate patients with a history of seizure disorders for worsened seizure control during hydrocodone bitartrate and acetaminophen tablet therapy.

Withdrawal

Do not rapidly reduce or abruptly discontinue hydrocodone bitartrate and acetaminophen tablets in a patient physically dependent on opioids. When discontinuing hydrocodone bitartrate and acetaminophen tablets in a physically dependent patient, gradually taper the dosage. Rapid tapering of hydrocodone bitartrate and acetaminophen tablets in a patient physically dependent on opioids may lead to a withdrawal syndrome and return of pain [see Dosage and Administration, Drug Abuse and Dependence].

Additionally, avoid the use of mixed agonist/antagonist (e.g., pentazocine, nalbuphine, and butorphanol) or partial agonist (e.g., buprenorphine) analgesics in patients who are receiving a full opioid agonist analgesic, including hydrocodone bitartrate and acetaminophen tablets. In these patients, mixed agonist/antagonist and partial agonist analgesics may reduce the analgesic effect and/or precipitate withdrawal symptoms [see Precautions/Drug Interactions].

PRECAUTIONS

Risks of Driving and Operating Machinery

Hydrocodone Bitartrate and Acetaminophen Tablets may impair the mental or physical abilities needed to perform potentially hazardous activities such as driving a car or operating machinery. Warn patients not to drive or operate dangerous machinery unless they are tolerant to the effects of Hydrocodone Bitartrate and Acetaminophen Tablets and know how they will react to the medication [see Precautions; Information for Patients].

INFORMATION FOR PATIENTS/CAREGIVERS

Advise the patient to read the FDA-approved patient labeling (Medication Guide).

Storage and Disposal

Because of the risks associated with accidental ingestion, misuse, and abuse, advise patients to store hydrocodone bitartrate and acetaminophen tablets securely, out of sight and reach of children, and in a location not accessible by others, including visitors to the home. Inform patients that leaving hydrocodone bitartrate and acetaminophen tablets unsecured can pose a deadly risk to others in the home [see Warnings, Drug Abuse and Dependence].

Advise patients and caregivers that when medicines are no longer needed, they should be disposed of promptly. Expired, unwanted, or unused hydrocodone bitartrate and acetaminophen tablets should be disposed of by flushing the unused medication down the toilet if a drug take-back option is not readily available. Inform patients that they can visit www.fda.gov/drugdisposal for a complete list of medicines recommended for disposal by flushing, as well as additional information on disposal of unused medicines.

Addiction, Abuse, and Misuse

Inform patients that the use of Hydrocodone Bitartrate and Acetaminophen Tablets, even when taken as recommended, can result in addiction, abuse, and misuse, which can lead to overdose and death [see Warnings]. Instruct patients not to share Hydrocodone Bitartrate and Acetaminophen Tablets with others and to take steps to protect Hydrocodone Bitartrate and Acetaminophen Tablets from theft or misuse.

Life-Threatening Respiratory Depression

Inform patients of the risk of life-threatening respiratory depression, including information that the risk is greatest when starting Hydrocodone Bitartrate and Acetaminophen Tablets or when the dosage is increased, and that it can occur even at recommended dosages.

Educate patients and caregivers on how to recognize respiratory depression and emphasize the importance of calling 911 or getting emergency medical help right away in the event of a known or suspected overdose [see Warnings, Life Threatening Respiratory Depression].

Accidental Ingestion

Inform patients that accidental ingestion, especially by children, may result in respiratory depression or death [see Warnings].

Interactions with Benzodiazepines and Other CNS Depressants

Inform patients and caregivers that potentially fatal additive effects may occur if Hydrocodone Bitartrate and Acetaminophen Tablets are used with benzodiazepines or other CNS depressants, including alcohol (e.g., non-benzodiazepine sedative/hypnotics, anxiolytics, tranquilizers, muscle relaxants, general anesthetics, antipsychotics, gabapentinoids [gabapentin or pregabalin], and other opioids), and not to use these concomitantly unless supervised by a healthcare provider [see Warnings, Precautions; Drug Interactions].

Patient Access to an Opioid Overdose Reversal Agent for the Emergency Treatment of Opioid Overdose

Inform patients and caregivers about opioid overdose reversal agents (e.g., naloxone, nalmefene). Discuss the importance of having access to an opioid overdose reversal agent, especially if the patient has risk factors for overdose (e.g., concomitant use of CNS depressants, a history of opioid use disorder, or prior opioid overdose) or if there are household members (including children) or other close contacts at risk for accidental ingestion or opioid overdose.

Discuss with the patient the options for obtaining an opioid overdose reversal agent (e.g., prescription, over-the-counter, or as part of a community-based program) [see WARNINGS, DOSAGE AND ADMINISTRATION].

Educate patients and caregivers on how to recognize the signs and symptoms of an overdose.

Explain to patients and caregivers that effects of opioid overdose reversal agents like naloxone and nalmefene are temporary, and that they must call 911 or get emergency medical help right away in all cases of known or suspected opioid overdose, even if an opioid overdose reversal agent is administered [see OVERDOSAGE].

Advise patients and caregivers:

- how to treat with the overdose reversal agent in the event of an opioid overdose.
- to tell family and friends about their opioid overdose reversal agent and to keep it in a place where family and friends can access it in an emergency
- to read the Patient Information (or other educational material) that will come with their opioid overdose reversal agent. Emphasize the importance of doing this before an opioid emergency happens, so the patient and caregiver will know what to do.

Hyperalgesia and Allodynia

Inform patients and caregivers not to increase opioid dosage without first consulting a clinician. Advise patients to seek medical attention if they experience symptoms of hyperalgesia, including worsening pain, increased sensitivity to pain, or new pain [see Warnings; Adverse Reactions].

Serotonin Syndrome

Inform patients that Hydrocodone Bitartrate and Acetaminophen Tablets could cause a rare but potentially life-threatening condition resulting from concomitant administration of serotonergic drugs. Warn patients of the symptoms of serotonin syndrome and to seek medical attention right away if symptoms develop. Instruct patients to inform their healthcare providers if they are taking, or plan to take serotonergic medications [see Precautions; Drug Interactions].

Monoamine Oxidase Inhibitor (MAOI) Interaction

Inform patients to avoid taking Hydrocodone and Acetaminophen Tablets while using any drugs that inhibit monoamine oxidase. Patients should not start MAOIs while taking Hydrocodone and Acetaminophen Tablets [see Precautions; Drug Interactions].

Important Administration Instructions

Instruct patients how to properly take Hydrocodone Bitartrate and Acetaminophen Tablets [see Dosage and Administration, Warnings].

Important Discontinuation Instructions

In order to avoid developing withdrawal symptoms, instruct patients not to discontinue hydrocodone bitartrate and acetaminophen tablets without first discussing a tapering plan with the prescriber [see Dosage and Administration].

Maximum Daily Dose of Acetaminophen

Inform patients not to take more than 4000 milligrams of acetaminophen per day. Advise patients to call their prescriber if they take more than the recommended dose.

Driving or Operating Heavy Machinery

Inform patients that Hydrocodone Bitartrate and Acetaminophen Tablets may impair the ability to perform potentially hazardous activities such as driving a car or operating heavy machinery. Advise patients not to perform such tasks until they know how they will react to the medication [see Warnings].

Constipation

Advise patients of the potential for severe constipation, including management instructions and when to seek medical attention [see Adverse Reactions, Clinical Pharmacology].

Adrenal Insufficiency

Inform patients that Hydrocodone Bitartrate and Acetaminophen Tablets opioids could cause adrenal insufficiency, a potentially life-threatening condition. Adrenal insufficiency may present with non-specific symptoms and signs such as nausea, vomiting, anorexia, fatigue, weakness, dizziness, and low blood pressure. Advise patients to seek medical attention if they experience a constellation of these symptoms [see Warnings].

Hypotension

Inform patients that Hydrocodone Bitartrate and Acetaminophen Tablets may cause orthostatic hypotension and syncope. Instruct patients how to recognize symptoms of low blood pressure and how to reduce the risk of serious consequences should hypotension occur (e.g., sit or lie down, carefully rise from a sitting or lying position) [see Warnings].

Anaphylaxis

Inform patients that anaphylaxis has been reported with ingredients contained in Hydrocodone Bitartrate and Acetaminophen Tablets. Advise patients how to recognize such a reaction and when to seek medical attention [see Contraindications, Adverse Reactions].

Pregnancy

Neonatal Opioid Withdrawal Syndrome

Inform female patients of reproductive potential that use of Hydrocodone Bitartrate and Acetaminophen Tablets for an extended period of time during pregnancy can result in neonatal opioid withdrawal syndrome, which may be life-threatening if not recognized and treated [see Warnings, Precautions; Pregnancy].

Embryo-Fetal Toxicity

Inform female patients of reproductive potential that Hydrocodone Bitartrate and Acetaminophen Tablets can cause fetal harm and to inform their healthcare provider of a known or suspected pregnancy [see Precautions; Pregnancy].

Lactation

Advise nursing mothers to carefully observe infants for increased sleepiness (more than usual), breathing difficulties, or limpness. Instruct nursing mothers to seek immediate medical care if they notice these signs [see Precautions; Nursing Mothers].

Infertility

Inform patients that use of opioids for an extended period of time may cause reduced fertility. It is not known whether these effects on fertility are reversible [see Adverse Reactions].

Laboratory Tests

In patients with severe hepatic or renal disease, effects of therapy should be followed with serial liver and/or renal function tests.

DRUG INTERACTIONS

Inhibitors of CYP3A4 and CYP2D6

The concomitant use of Hydrocodone Bitartrate and Acetaminophen Tablets and CYP3A4 inhibitors, such as macrolide antibiotics (e.g., erythromycin), azole-antifungal agents (e.g. ketoconazole), and protease inhibitors (e.g., ritonavir), can increase the plasma concentration of the hydrocodone from Hydrocodone Bitartrate and Acetaminophen Tablets, resulting in increased or prolonged opioid effects. These effects could be more pronounced with concomitant use of Hydrocodone Bitartrate and Acetaminophen Tablets and both CYP3A4 and CYP2D6 inhibitors, particularly when an inhibitor is added after a stable dose of Hydrocodone Bitartrate and Acetaminophen Tablets is achieved [see Warnings].

After stopping a CYP3A4 inhibitor, as the effects of the inhibitor decline, the hydrocodone plasma concentration will decrease [see Clinical Pharmacology], resulting in decreased opioid efficacy or a withdrawal syndrome in patients who had developed physical dependence to Hydrocodone Bitartrate and Acetaminophen Tablets.

If concomitant use is necessary, consider dosage reduction of Hydrocodone Bitartrate and Acetaminophen Tablets until stable drug effects are achieved. Evaluate patients at frequent intervals for respiratory depression and sedation. If a CYP3A4 inhibitor is discontinued, consider increasing the Hydrocodone Bitartrate and Acetaminophen Tablets dosage until stable drug effects are achieved. Evaluate for signs or symptoms of opioid withdrawal.

Inducers of CYP3A4

The concomitant use of Hydrocodone Bitartrate and Acetaminophen Tablets and CYP3A4 inducers, such as rifampin, carbamazepine, and phenytoin, can decrease the plasma concentration of hydrocodone [see Clinical Pharmacology], resulting in decreased efficacy or onset of a withdrawal syndrome in patients who have developed physical dependence to hydrocodone [see Warnings].

After stopping a CYP3A4 inducer, as the effects of the inducer decline, the hydrocodone plasma concentration will increase [see Clinical Pharmacology], which could increase or prolong both the therapeutic effects and adverse reactions and may cause serious respiratory depression.

If concomitant use is necessary, consider increasing the Hydrocodone Bitartrate and Acetaminophen Tablets dosage until stable drug effects are achieved. Evaluate the patient for signs and symptoms of opioid withdrawal. If a CYP3A4 inducer is discontinued, consider Hydrocodone Bitartrate and Acetaminophen Tablets dosage reduction and evaluate patients at frequent intervals for signs of respiratory depression and sedation.

Benzodiazepines and Other Central Nervous System (CNS) Depressants

Due to additive pharmacologic effect, the concomitant use of benzodiazepines or other CNS depressants, such as benzodiazepines and other sedative/hypnotics, anxiolytics, and tranquilizers, muscle relaxants, general anesthetics, antipsychotics, gabapentinoids [gabapentin or pregabalin], and other opioids, including alcohol, can increase the risk of hypotension, respiratory depression, profound sedation, coma, and death.

Reserve concomitant prescribing of these drugs for use in patients for whom alternative treatment options are inadequate. Limit dosages and durations to the minimum required. Inform patients and caregivers of this potential interaction, educate them on the signs and symptoms of respiratory depression (including sedation). If concomitant use is warranted, consider recommending or prescribing an opioid overdose reversal agent [see WARNINGS, DOSAGE AND ADMINISTRATION].

Serotonergic Drugs

The concomitant use of opioids with other drugs that affect the serotonergic neurotransmitter system, such as selective serotonin reuptake inhibitors (SSRIs), serotonin and norepinephrine reuptake inhibitors (SNRIs), tricyclic antidepressants (TCAs), triptans, 5-HT3 receptor antagonists, drugs that affect the serotonin neurotransmitter system (e.g., mirtazapine, trazodone, tramadol), certain muscle relaxants (i.e., cyclobenzaprine, metaxalone), and monoamine oxidase (MAO) inhibitors (those intended to treat psychiatric disorders and also others, such as linezolid and intravenous methylene blue), has resulted in serotonin syndrome [see Precautions; Information for Patients].

If concomitant use is warranted, frequently evaluate the patient, particularly during treatment initiation and dose adjustment. Discontinue Hydrocodone Bitartrate and Acetaminophen Tablets if serotonin syndrome is suspected.

Monoamine Oxidase Inhibitors (MAOIs)

The concomitant use of opioids and MAOIs, such as phenelzine, tranylcypromine, or linezolid, may manifest as serotonin syndrome, or opioid toxicity (e.g., respiratory depression, coma) [see Warnings].

The use of Hydrocodone Bitartrate and Acetaminophen Tablets is not recommended for patients taking MAOIs or within 14 days of stopping such treatment.

If urgent use of an opioid is necessary, use test doses and frequent titration of small doses to treat pain while closely monitoring blood pressure and signs and symptoms of CNS and respiratory depression.

Mixed Agonist/Antagonist and Partial Agonist Opioid Analgesics

The concomitant use of opioids with other opioid analgesics, such as butorphanol, nalbuphine, pentazocine, may reduce the analgesic effect of Hydrocodone Bitartrate and Acetaminophen Tablets and/or precipitate withdrawal symptoms.

Advise patient to avoid concomitant use of these drugs.

Muscle Relaxants

Hydrocodone Bitartrate and Acetaminophen Tablets may enhance the neuromuscular blocking action of skeletal muscle relaxants and produce an increased degree of respiratory depression.

If concomitant use is warranted, because respiratory depression that may be greater than otherwise expected and decrease the dosage of Hydrocodone Bitartrate and Acetaminophen Tablets and/or the muscle relaxant (e.g., cyclobenzaprine, metaxalone) as necessary. Due to the risk of respiratory depression with concomitant use of muscle relaxants and opioids, consider recommending or prescribing an opioid overdose reversal agent [see WARNINGS, DOSAGE AND ADMINISTRATION].

Diuretics

Opioids can reduce the efficacy of diuretics by inducing the release of antidiuretic hormone.

If concomitant use is warranted, evaluate patients for signs of diminished diuresis and/or effects on blood pressure and increase the dosage of the diuretic as needed.

Anticholinergic Drugs

The concomitant use of anticholinergic drugs may increase risk of urinary retention and/or severe constipation, which may lead to paralytic ileus.

If concomitant use is warranted, evaluate patients for signs of urinary retention or reduced gastric motility when Hydrocodone Bitartrate and Acetaminophen Tablets are used concomitantly with anticholinergic drugs.

Drug/Laboratory Test Interactions

Acetaminophen may produce false-positive test results for urinary 5-hydroxyindoleacetic acid.

Carcinogenesis, Mutagenesis, Impairment of Fertility

Carcinogenesis

Long-term studies to evaluate the carcinogenic potential of the combination of Hydrocodone Bitartrate and Acetaminophen Tablets have not been conducted.

Long-term studies in mice and rats have been completed by the National Toxicology Program to evaluate the carcinogenic potential of acetaminophen. In 2-year feeding studies, F344/N rats and B6C3F1 mice were fed a diet containing acetaminophen up to 6000 ppm. Female rats demonstrated equivocal evidence of carcinogenic activity based on increased incidences of mononuclear cell leukemia at 0.8 times the maximum human daily dose (MHDD) of 4 grams/day, based on a body surface area comparison. In contrast, there was no evidence of carcinogenic activity in male rats that received up to 0.7 times or mice at up to 1.2-1.4 times the MHDD, based on a body surface area comparison.

Mutagenesis

In the published literature, acetaminophen has been reported to be clastogenic when administered at 1500 mg/kg/day to the rat model (3.6-times the MHDD, based on a body surface area comparison). In contrast, no clastogenicity was noted at a dose of 750 mg/kg/day (1.8-times the MHDD, based on a body surface area comparison), suggesting a threshold effect.

Impairment of Fertility

In studies conducted by the National Toxicology Program, fertility assessments with acetaminophen have been completed in Swiss CD-1 mice via a continuous breeding study. There were no effects on fertility parameters in mice consuming up to 1.7 times the MHDD of acetaminophen, based on a body surface area comparison.

Although there was no effect on sperm motility or sperm density in the epididymis, there was a significant increase in the percentage of abnormal sperm in mice consuming 1.78 times the MHDD (based on a body surface comparison) and there was a reduction in the number of mating pairs producing a fifth litter at this dose, suggesting the potential for cumulative toxicity with chronic administration of acetaminophen near the upper limit of daily dosing.

Published studies in rodents report that oral acetaminophen treatment of male animals at doses that are 1.2 times the MHDD and greater (based on a body surface comparison) result in decreased testicular weights, reduced spermatogenesis, reduced fertility, and reduced implantation sites in females given the same doses. These effects appear to increase with the duration of treatment. The clinical significance of these findings is not known.

Infertility

Use of opioids for an extended period of time may cause reduced fertility in females and males of reproductive potential. It is not known whether these effects on fertility are reversible [see Adverse Reactions].

Pregnancy

There are no adequate and well-controlled studies in pregnant women. Hydrocodone Bitartrate and Acetaminophen Tablets should be used during pregnancy only if the potential benefit justifies the potential risk to the fetus.

Nonteratogenic Effects

Fetal/Neonatal Adverse Reactions

Use of opioid analgesics for an extended period of time pregnancy for medical or nonmedical purposes can result in physical dependence in the neonate and neonatal opioid withdrawal syndrome shortly after birth.

Neonatal opioid withdrawal syndrome presents as irritability, hyperactivity, abnormal sleep pattern, high pitched cry, tremor, vomiting, diarrhea and failure to gain weight. The onset, duration, and severity of neonatal opioid withdrawal syndrome vary based on the specific opioid used, duration of use, timing and amount of last maternal use, and rate of elimination of the drug by the newborn. Observe newborns for symptoms of neonatal opioid withdrawal syndrome and manage accordingly [see Warnings].

Labor or Delivery

Opioids cross the placenta and may produce respiratory depression and psycho-physiologic effects in neonates. An opioid overdose reversal agent, such as naloxone or nalmefene, must be available for reversal of opioid-induced respiratory depression in the neonate. Hydrocodone Bitartrate and Acetaminophen Tablets are not recommended for use in pregnant women during or immediately prior to labor, when other analgesic techniques are more appropriate. Opioid analgesics, including Hydrocodone Bitartrate and Acetaminophen Tablets, can prolong labor through actions which temporarily reduce the strength, duration, and frequency of uterine contractions. However, this effect is not consistent and may be offset by an increased rate of cervical dilation, which tends to shorten labor. Monitor neonates exposed to opioid analgesics during labor for signs of excess sedation and respiratory depression.

Nursing Mothers

Hydrocodone is present in human milk.

The developmental and health benefits of breastfeeding should be considered along with the mother's clinical need for Hydrocodone Bitartrate and Acetaminophen Tablets and any potential adverse effects on the breastfed infant from Hydrocodone Bitartrate and Acetaminophen Tablets or from the underlying maternal condition.

Infants exposed to Hydrocodone Bitartrate and Acetaminophen Tablets through breast milk should be monitored for excess sedation and respiratory depression. Withdrawal symptoms can occur in breastfed infants when maternal administration of an opioid analgesic is stopped, or when breast-feeding is stopped.

Pediatric Use

Safety and effectiveness of Hydrocodone Bitartrate and Acetaminophen Tablets in pediatric patients have not been established.

Geriatric Use

Elderly patients (aged 65 years or older) may have increased sensitivity to Hydrocodone Bitartrate and Acetaminophen Tablets. In general, use caution when selecting a dosage for an elderly patient, usually starting at the low end of the dosing range, reflecting the greater frequency of decreased hepatic, renal, or cardiac function and of concomitant disease or other drug therapy.

Respiratory depression is the chief risk for elderly patients treated with opioids, and has occurred after large initial doses were administered to patients who were not opioid-tolerant or when opioids were co-administered with other agents that depress respiration. Titrate the dosage of Hydrocodone Bitartrate and Acetaminophen Tablets slowly in geriatric patients and frequently reevaluate the patient for signs of central nervous system and respiratory depression [see Warnings].

Hydrocodone and acetaminophen are known to be substantially excreted by the kidney, and the risk of adverse reactions to this drug may be greater in patients with impaired renal function. Because elderly patients are more likely to have decreased renal function, care should be taken in dose selection, and it may be useful to regularly evaluate renal function.

Hepatic Impairment

Patients with hepatic impairment may have higher plasma hydrocodone concentrations than those with normal function. Use a low initial dose of Hydrocodone Bitartrate and Acetaminophen Tablets in patients with hepatic impairment and follow closely for adverse events such as respiratory depression and sedation.

Renal Impairment

Patients with renal impairment may have higher plasma hydrocodone concentrations than those with normal function. Use a low initial dose Hydrocodone Bitartrate and Acetaminophen Tablets in patients with renal impairment and follow closely for adverse events such as respiratory depression and sedation.

ADVERSE REACTIONS

The following adverse reactions have been identified during post approval use of hydrocodone and acetaminophen tablets. Because these reactions are reported voluntarily from a population of uncertain size, it is not always possible to reliably estimate their frequency or establish a causal relationship to drug exposure.

The most frequently reported adverse reactions are light-headedness, dizziness, sedation, nausea and vomiting. Other adverse reactions include:

Central Nervous System – Drowsiness, mental clouding, lethargy, impairment of mental and physical performance, anxiety, fear, dysphoria, psychological dependence, mood changes.

Gastrointestinal System –Constipation.

Genitourinary System – Ureteral spasm, spasm of vesical sphincters, and urinary retention.

Special Senses – Cases of Hearing impairment, or permanent loss have been reported predominately in patients with chronic overdose.

Dermatological – Skin rash, pruritus, Stevens-Johnson syndrome, toxic epidermal necrolysis, allergic reactions

Hematological - Thrombocytopenia, agranulocytosis.

- Serotonin syndrome: Cases of serotonin syndrome, a potentially life-threatening condition, have been reported during concomitant use of opioids with serotonergic drugs.
- Adrenal insufficiency: Cases of adrenal insufficiency have been reported with opioid use, more often following greater than one month of use.
- Anaphylaxis: Anaphylaxis has been reported with ingredients contained in Hydrocodone Bitartrate and Acetaminophen Tablets.
- Androgen deficiency: Cases of androgen deficiency have occurred with use of opioids for an extended period of time [see Clinical Pharmacology].
- Hyperalgesia and Allodynia: Cases of hyperalgesia and allodynia have been reported with opioid therapy of any duration [see Warnings].
- Hypoglycemia: Cases of hypoglycemia have been reported in patients taking opioids. Most reports were in patients with at least one predisposing risk factor (e.g., diabetes).

Opioid-induced esophageal dysfunction (OIED): Cases of OIED have been reported in patients taking opioids and may occur more frequently in patients taking higher doses of opioids, and/or in patients taking opioids longer term [see WARNINGS].

Adverse Reactions from Observational Studies

A prospective, observational cohort study estimated the risks of addiction, abuse, and misuse in patients initiating long-term use of Schedule II opioid analgesics between 2017 and 2021. Study participants included in one or more analyses had been enrolled in selected insurance plans or health systems for at least one year, were free of at least one outcome at baseline, completed a minimum number of follow-up assessments, and either: 1) filled multiple extended-release/long-acting opioid analgesic prescriptions during a 90 day period (n=978); or 2) filled any Schedule II opioid analgesic prescriptions covering at least 70 of 90 days (n=1,244). Those included also had no dispensing of the qualifying opioids in the previous 6 months.

Over 12 months:

- approximately 1% to 6% of participants across the two cohorts newly met criteria for addiction, as assessed with two validated interview-based measures of moderate-to-severe opioid use disorder based on Diagnostic and Statistical Manual of Mental Disorders, Fifth Edition (DSM-5) criteria, and
- approximately 9% and 22% of participants across the two cohorts newly met criteria for prescription opioid abuse and misuse [defined in DRUG ABUSE AND DEPENDENCE], respectively, as measured with a validated self-reported instrument.

A retrospective, observational cohort study estimated the risk of opioid involved overdose or opioid overdose-related death in patients with new long-term use of Schedule II opioid analgesics from 2006 through 2016 (n=220,249). Included patients had been enrolled in either one of two commercial insurance programs, one managed care program, or one Medicaid program for at least 9 months. New long-term use was defined as having Schedule II opioid analgesic prescriptions covering at least 70 days' supply over the 3 months prior to study entry and none during the preceding 6 months. Patients were excluded if they had an opioid-involved overdose in the 9 months prior to study entry. Overdose was measured using a validated medical code-based algorithm with linkage to the National Death Index database. The 5-year cumulative incidence estimates for opioid-involved overdose or opioid overdose-related death ranged from approximately 1.5% to 4% across study sites, counting only the first event during follow-up. Approximately 17% of first opioid overdoses observed over the entire study period (5-11 years, depending on the study site) were fatal. Higher baseline opioid dose was the strongest and most consistent predictor of opioid-involved overdose or opioid overdose-related death. Study exclusion criteria may have selected patients at lower risk of overdose, and substantial loss to follow-up (approximately 80%) also may have biased estimates.

The risk estimates from the studies described above may not be generalizable to all patients receiving opioid analgesics, such as those with exposures shorter or longer than the duration evaluated in the studies.

To report SUSPECTED ADVERSE REACTIONS, contact Strides Pharma Inc. at 1-877-244-9825 or FDA at 1-800-FDA-1088 or www.fda.gov/medwatch.

DRUG ABUSE AND DEPENDENCE

Controlled Substance

Hydrocodone Bitartrate and Acetaminophen Tablets contain hydrocodone, a Schedule II controlled substance.

Abuse

Hydrocodone Bitartrate and acetaminophen tablets contain hydrocodone, a substance with a high potential for misuse and abuse, which can lead to the development of substance use disorder, including addiction [see Warnings].

Misuse is the intentional use, for therapeutic purposes, of a drug by an individual in a way other than prescribed by a healthcare provider or for whom it was not prescribed.

Abuse is the intentional, non-therapeutic use of a drug, even once, for its desirable psychological or physiological effects.

Drug addiction is a cluster of behavioral, cognitive, and physiological phenomena that may include a strong desire to take the drug, difficulties in controlling drug use (e.g., continuing drug use despite harmful consequences, giving a higher priority to drug use than other activities and obligations), and possible tolerance or physical dependence.

Misuse and abuse of Hydrocodone Bitartrate and acetaminophen tablets increases risk of overdose, which may lead to central nervous system and respiratory depression, hypotension, seizures, and death. The risk is increased with concurrent abuse of Hydrocodone Bitartrate and acetaminophen tablets with alcohol and other CNS depressants. Abuse of and addiction to opioids in some individuals may not be accompanied by concurrent tolerance and symptoms of physical dependence. In addition, abuse of opioids can occur in the absence of addiction.

All patients treated with opioids require careful and frequent reevaluation for signs of misuse, abuse, and addiction, because use of opioid analgesic products carries the risk of addiction even under appropriate medical use. Patients at high risk of Hydrocodone Bitartrate and acetaminophen tablets abuse include those with a history of prolonged use of any opioid, including products containing Hydrocodone Bitartrate and acetaminophen, those with a history of drug or alcohol abuse, or those who use Hydrocodone Bitartrate and acetaminophen tablets in combination with other abused drugs.

"Drug-seeking" behavior is very common in persons with substance use disorders. Drug-seeking tactics include emergency calls or visits near the end of office hours, refusal to undergo appropriate examination, testing, or referral, repeated "loss" of prescriptions, tampering with prescriptions, and reluctance to provide prior medical records or contact information for other treating healthcare provider(s). "Doctor shopping" (visiting multiple prescribers to obtain additional prescriptions) is common among people who abuse drugs and people with substance use disorder. Preoccupation with achieving adequate pain relief can be appropriate behavior in a patient with inadequate pain control.

Hydrocodone Bitartrate and acetaminophen tablets, like other opioids, can be diverted for nonmedical use into illicit channels of distribution. Careful record-keeping of prescribing information, including quantity, frequency, and renewal requests, as required by state and federal law, is strongly advised.

Proper assessment of the patient, proper prescribing practices, periodic reevaluation of therapy, and proper dispensing and storage are appropriate measures that help to limit abuse of opioid drugs.

Risks Specific to Abuse of Hydrocodone Bitartrate and Acetaminophen Tablets

Abuse of Hydrocodone bitartrate and acetaminophen tablets poses a risk of overdose and death. The risk is increased with concurrent use of Hydrocodone bitartrate and acetaminophen tablets with alcohol and/or other CNS depressants.

Parenteral drug abuse is commonly associated with transmission of infectious diseases such as hepatitis and HIV.

Dependence

Both tolerance and physical dependence can develop during use of opioid therapy.

Tolerance is a physiological state characterized by a reduced response to a drug after repeated administration (i.e., a higher dose of a drug is required to produce the same effect that was once obtained at a lower dose).

Physical dependence is a state that develops as a result of a physiological adaptation in response to repeated drug use, manifested by withdrawal signs and symptoms after abrupt discontinuation or a significant dose reduction of a drug.

Withdrawal may be precipitated through the administration of drugs with opioid antagonist activity (e.g., naloxone, nalmefene), mixed agonist/antagonist analgesics (e.g., pentazocine, butorphanol, nalbuphine), or partial agonists (e.g., buprenorphine). Physical dependence may not occur to a clinically significant degree until after several days to weeks of continued use.

Do not rapidly reduce or abruptly discontinue Hydrocodone Bitartrate and Acetaminophen Tablets in a patient physically dependent on opioids. Rapid tapering of Hydrocodone Bitartrate and Acetaminophen Tablets in a patient physically dependent on opioids may lead to serious withdrawal symptoms, uncontrolled pain, and suicide. Rapid discontinuation has also been associated with attempts to find other sources of opioid analgesics, which may be confused with drug-seeking for abuse.

When discontinuing Hydrocodone Bitartrate and Acetaminophen Tablets, gradually taper the dosage using a patient-specific plan that considers the following: the dose of Hydrocodone Bitartrate and Acetaminophen Tablets the patient has been taking, the duration of treatment, and the physical and psychological attributes of the patient. To improve the likelihood of a successful taper and minimize withdrawal symptoms, it is important that the opioid tapering schedule is agreed upon by the patient. In patients taking opioids for an extended period of time at high doses, ensure that a multimodal approach to pain management, including mental health support (if needed), is in place prior to initiating an opioid analgesic taper [see Dosage and Administration, and Warnings].

Infants born to mothers physically dependent on opioids will also be physically dependent and may exhibit respiratory difficulties and withdrawal signs [see Pregnancy].

OVERDOSAGE

Following an acute overdosage, toxicity may result from hydrocodone or acetaminophen.

Clinical Presentation

Acute overdose with Hydrocodone Bitartrate and Acetaminophen Tablets can be manifested by respiratory depression, somnolence progressing to stupor or coma, skeletal muscle flaccidity, cold and clammy skin, constricted pupils, and, in some cases, pulmonary edema, bradycardia, hypotension, hypoglycemia, partial or complete airway obstruction, atypical snoring, and death. Marked mydriasis rather than miosis may be seen with hypoxia in overdose situations [see CLINICAL PHARMACOLOGY]. Toxic leukoencephalopathy has been reported after opioid overdose and can present hours, days, or weeks after apparent recovery from the initial intoxication.

Acetaminophen

Dose-dependent, potentially fatal hepatic necrosis is the most serious adverse effect of acetaminophen overdosage. Renal tubular necrosis, hypoglycemic coma and coagulation defects may also occur.

Early symptoms following a potentially hepatotoxic overdose may include: nausea, vomiting, diaphoresis and general malaise. Clinical and laboratory evidence of hepatic toxicity may not be apparent until 48 to 72 hours post-ingestion.

Treatment of Overdose

Hydrocodone

In case of overdose, priorities are the reestablishment of a patent and protected airway and institution of assisted or controlled ventilation, if needed. Employ other supportive measures (including oxygen and vasopressors) in the management of circulatory shock and pulmonary edema as indicated. Cardiac arrest or arrhythmias will require advanced life-support measures.

For clinically significant respiratory or circulatory depression secondary to opioid overdose, administer an opioid overdose reversal agent such as naloxone or nalmefene.

Because the duration of opioid reversal is expected to be less than the duration of action of hydrocodone in Hydrocodone Bitartrate and Acetaminophen Tablets, carefully monitor the patient until spontaneous respiration is reliably reestablished. If the response to an opioid overdose reversal agent is suboptimal or only brief in nature, administer additional reversal agent as directed by the product's prescribing information.

In an individual physically dependent on opioids, administration of the recommended usual dosage of the opioid overdose reversal agent will precipitate an acute withdrawal syndrome. The severity of the withdrawal symptoms experienced will depend on the degree of physical dependence and the dose of the reversal agent administered. If a decision is made to treat serious respiratory depression in the physically dependent patient, administration of the reversal agent should be initiated with care and by titration with smaller than usual doses of the reversal agent.

Acetaminophen

Gastric decontamination with activated charcoal should be administered just prior to N-acetylcysteine (NAC) to decrease systemic absorption if acetaminophen ingestion is known or suspected to have occurred within a few hours of presentation. Serum acetaminophen levels should be obtained immediately if the patient presents 4 hours or more after ingestion to assess potential risk of hepatotoxicity; acetaminophen levels drawn less than 4 hours post-ingestion may be misleading. To obtain the best possible outcome, NAC should be administered as soon as possible where impending or evolving liver injury is suspected. Intravenous NAC may be administered when circumstances preclude oral administration.

Vigorous supportive therapy is required in severe intoxication. Procedures to limit the continuing absorption of the drug must be readily performed since the hepatic injury is dose dependent and occurs early in the course of intoxication.

DOSAGE AND ADMINISTRATION

Important Dosage and Administration Instructions

Hydrocodone Bitartrate and Acetaminophen tablets should be prescribed only by healthcare professionals who are knowledgeable about the use of opioids and how to mitigate the associated risks.

Use the lowest effective dosage for the shortest duration of time consistent with individual patient treatment goals [see Warnings]. Because the risk of overdose increases as opioid doses increase, reserve titration to higher doses of Hydrocodone Bitartrate and Acetaminophen tablets for patients in whom lower doses are insufficiently effective and in whom the expected benefits of using a higher dose opioid clearly outweigh the substantial risks.

Many acute pain conditions (e.g., the pain that occurs with a number of surgical procedures or acute musculoskeletal injuries) require no more than a few days of an opioid analgesic. Clinical guidelines on opioid prescribing for some acute pain conditions are available.

There is variability in the opioid analgesic dose and duration needed to adequately manage pain due both to the cause of pain and to individual patient factors. Initiate the dosing regimen for each patient individually, taking into account the patient's underlying cause and severity of pain, prior analgesic treatment and response, and risk factors for addiction, abuse, and misuse [see Warnings].

Respiratory depression can occur at any time during opioid therapy, especially when initiating and following dosage increases with Hydrocodone Bitartrate and Acetaminophen tablets. Consider this risk when selecting an initial dose and when making dose adjustments [see Warnings].

Patient Access to an Opioid Overdose Reversal Agent for the Emergency Treatment of Opioid Overdose

Inform patients and caregivers about opioid overdose reversal agents (e.g., naloxone, nalmefene). Discuss the importance of having access to an opioid overdose reversal agent, especially if the patient has risk factors for overdose (e.g., concomitant use of CNS depressants, a history of opioid use disorder, or prior opioid overdose) or if there are household members (including children) or other close contacts at risk for accidental ingestion or opioid overdose. The presence of risk factors for overdose should not prevent the management of pain in any patient [see WARNINGS; Addiction, Abuse, and Misuse; Life-Threatening Respiratory Depression; Risks from Concomitant Use with Benzodiazepines or Other CNS Depressants].

Discuss the options for obtaining an opioid overdose reversal agent (e.g., prescription, over-the-counter, or as part of a community-based program).

There are important differences among the opioid overdose reversal agents, such as route of administration, product strength, approved patient age range, and pharmacokinetics. Be familiar with these differences, as outlined in the approved labeling for those products, prior to recommending or prescribing such an agent.

Initial Dosage

Use of Hydrocodone Bitartrate and Acetaminophen Tablets as the First Opioid Analgesic

5 mg/325 mg | Initiate treatment with Hydrocodone Bitartrate and Acetaminophen tablets in a dosing range of 1 to 2 tablets every 4 to 6 hours as needed for pain, at the lowest dose necessary to achieve adequate analgesia. Titrate the dose based upon the individual patient's response to their initial dose of Hydrocodone Bitartrate and Acetaminophen tablets. The total daily dosage should not exceed 8 tablets.
7.5 mg/325 mg 10 mg/325 mg | Initiate treatment with Hydrocodone Bitartrate and Acetaminophen tablets with 1 tablet every 4 to 6 hours as needed for pain, at the lowest dose necessary to achieve adequate analgesia. Titrate the dose based upon the individual patient's response to their initial dose of Hydrocodone Bitartrate and Acetaminophen tablets. The total daily dosage should not exceed 6 tablets.

Conversion from Other Opioids to Hydrocodone Bitartrate and Acetaminophen Tablets

There is inter-patient variability in the potency of opioid drugs and opioid formulations. Therefore, a conservative approach is advised when determining the total daily dosage of Hydrocodone Bitartrate and Acetaminophen Tablets. It is safer to underestimate a patient's 24-hour Hydrocodone Bitartrate and Acetaminophen Tablets dosage than to overestimate the 24-hour Hydrocodone Bitartrate and Acetaminophen Tablets dosage and manage an adverse reaction due to overdose.

Conversion from Hydrocodone Bitartrate and Acetaminophen Tablets to Extended-Release Hydrocodone

The relative bioavailability of Hydrocodone Bitartrate and Acetaminophen Tablets compared to extended-release hydrocodone products is unknown, so conversion to extended release Hydrocodone products may lead to increased risk of excessive sedation and respiratory depression.

Titration and Maintenance of Therapy

Individually titrate Hydrocodone Bitartrate and Acetaminophen Tablets to a dose that provides adequate analgesia and minimizes adverse reactions. Continually reevaluate patients receiving Hydrocodone Bitartrate and Acetaminophen Tablets to assess the maintenance of pain control, signs and symptoms of opioid withdrawal, and other adverse reactions, as well as to reassess for the development of addiction, abuse, or misuse [see Warnings]. Frequent communication is important among the prescriber, other members of the healthcare team, the patient, and the caregiver/family during periods of changing analgesic requirements, including initial titration.

If the level of pain increases after dosage stabilization, attempt to identify the source of increased pain before increasing the Hydrocodone Bitartrate and Acetaminophen Tablets dosage. If after increasing the dosage, unacceptable opioid-related adverse reactions are observed (including an increase in pain after dosage increase), consider reducing the dosage [see Warnings]. Adjust the dosage to obtain an appropriate balance between management of pain and opioid-related adverse reactions.

Safe Reduction or Discontinuation of Hydrocodone Bitartrate and Acetaminophen Tablets

Do not rapidly reduce or abruptly discontinue hydrocodone bitartrate and acetaminophen tablets in patients who may be physically dependent on opioids. Rapid reduction or abrupt discontinuation of opioid analgesics in patients who are physically dependent on opioids has resulted in serious withdrawal symptoms, uncontrolled pain, and suicide. Rapid reduction or abrupt discontinuation has also been associated with attempts to find other sources of opioid analgesics, which may be confused with drug-seeking for abuse. Patients may also attempt to treat their pain or withdrawal symptoms with illicit opioids, such as heroin, and other substances.

When a decision has been made to decrease the dose or discontinue therapy in an opioid-dependent patient taking hydrocodone bitartrate and acetaminophen tablets, there are a variety of factors that should be considered, including the total daily dose of opioid (including hydrocodone bitartrate and acetaminophen tablets) the patient has been taking, the duration of treatment, the type of pain being treated, and the physical and psychological attributes of the patient. It is important to ensure ongoing care of the patient and to agree on an appropriate tapering schedule and follow-up plan so that patient and provider goals and expectations are clear and realistic. When opioid analgesics are being discontinued due to a suspected substance use disorder, evaluate and treat the patient, or refer for evaluation and treatment of the substance use disorder. Treatment should include evidence-based approaches, such as medication assisted treatment of opioid use disorder. Complex patients with co-morbid pain and substance use disorders may benefit from referral to a specialist.

There are no standard opioid tapering schedules that are suitable for all patients. Good clinical practice dictates a patient-specific plan to taper the dose of the opioid gradually. For patients on hydrocodone bitartrate and acetaminophen tablets who are physically opioid-dependent, initiate the taper by a small enough increment (e.g., no greater than 10% to 25% of the total daily dose) to avoid withdrawal symptoms, and proceed with dose-lowering at an interval of every 2 to 4 weeks. Patients who have been taking opioids for briefer periods of time may tolerate a more rapid taper.

It may be necessary to provide the patient with lower dosage strengths to accomplish a successful taper. Reassess the patient frequently to manage pain and withdrawal symptoms, should they emerge. Common withdrawal symptoms include restlessness, lacrimation, rhinorrhea, yawning, perspiration, chills, myalgia, and mydriasis. Other signs and symptoms also may develop, including irritability, anxiety, backache, joint pain, weakness, abdominal cramps, insomnia, nausea, anorexia, vomiting, diarrhea, or increased blood pressure, respiratory rate, or heart rate. If withdrawal symptoms arise, it may be necessary to pause the taper for a period of time or raise the dose of the opioid analgesic to the previous dose, and then proceed with a slower taper. In addition, evaluate patients for any changes in mood, emergence of suicidal thoughts, or use of other substances.

When managing patients taking opioid analgesics, particularly those who have been treated for an extended period of time, and/or with high doses for chronic pain, ensure that a multimodal approach to pain management, including mental health support (if needed), is in place prior to initiating an opioid analgesic taper. A multimodal approach to pain management may optimize the treatment of chronic pain, as well as assist with the successful tapering of the opioid analgesic [see Warnings/Withdrawal, Drug Abuse And Dependence].

HOW SUPPLIED

Hydrocodone Bitartrate and Acetaminophen Tablets, USP are supplied as follows:

Hydrocodone Bitartrate and Acetaminophen Tablets, USP 5 mg/325 mg are supplied as white, capsule shaped tablets containing 5 mg hydrocodone bitartrate (WARNING: May be habit-forming) and 325 mg acetaminophen. Tablets are debossed "P" on one side and "36 04" on the other side, and are supplied

Bottles of 100 tablets 64380-440-01

Bottles of 500 tablets 64380-440-02

Hydrocodone Bitartrate and Acetaminophen Tablets, USP 7.5 mg/325 mg are supplied as white, capsule shaped tablets containing 7.5 mg hydrocodone bitartrate (WARNING: May be habit-forming) and 325 mg acetaminophen. Tablets are debossed "P" on one side and "36 05" on the other side, and are supplied

Bottles of 100 tablets 64380-441-01

Bottles of 500 tablets 64380-441-02

Hydrocodone Bitartrate and Acetaminophen Tablets, USP 10 mg/325 mg are supplied as white, capsule shaped tablets containing 10 mg hydrocodone bitartrate (WARNING: May be habit-forming) and 325 mg acetaminophen. Tablets are debossed "P" on one side and "36 01" on the other side, and are supplied

Bottles of 100 tablets 64380-442-01

Bottles of 500 tablets 64380-442-02

Store at 20° to 25°C (68° to 77°F) [see USP Controlled Room Temperature].

Dispense in a tight, light-resistant container as defined in the USP with a child-resistant closure.

Store hydrocodone bitartrate and acetaminophen tablets securely and dispose of properly [see Precautions; Information for Patients].

Distributed by:

Strides Pharma Inc.

Bridgewater, NJ 08807

Revised: 01/2026

SPL MEDGUIDE

Medication Guide
HYDROCODONE BITARTRATE (hye" droe koe' done bye tar' trate) AND ACETAMINOPHEN (a seet" a min' oh fen) TABLETS CII

Hydrocodone Bitartrate and Acetaminophen Tablets are:
● A strong prescription pain medicine that contains an opioid (narcotic) that is used to manage pain severe enough to require an opioid pain medicine, when other pain treatments such as non-opioid pain medicines do not treat your pain well enough or you cannot tolerate them.
● An opioid pain medicine that can put you at risk for overdose and death. Even if you take your dose correctly as prescribed you are at risk for opioid addiction, abuse, and misuse that can lead to death.

Important information about Hydrocodone Bitartrate and Acetaminophen Tablets:
● Get emergency help or call 911 right away if you take too much Hydrocodone Bitartrate and Acetaminophen Tablets (overdose). When you first start taking Hydrocodone Bitartrate and Acetaminophen Tablets, when your dose is changed, or if you take too much (overdose), serious or life-threatening breathing problems that can lead to death may occur. Ask your healthcare provider about medicines like naloxone or nalmefene that can be used in an emergency to reverse an opioid overdose.
● Taking Hydrocodone Bitartrate and Acetaminophen Tablets with other opioid medicines, benzodiazepines, gabapentinoids (gabapentin or pregabalin), alcohol, or other central nervous system depressants (including street drugs) can cause severe drowsiness, decreased awareness, breathing problems, coma, and death.
● Never give anyone else your Hydrocodone Bitartrate and Acetaminophen Tablets. They could die from taking it. Selling or giving away Hydrocodone Bitartrate and Acetaminophen Tablets is against the law.
● Store Hydrocodone Bitartrate and Acetaminophen Tablets securely, out of sight and reach of children, and in a location not accessible by others, including visitors to the home.

Do not take Hydrocodone Bitartrate and Acetaminophen Tablets if you have:
● severe asthma, trouble breathing, or other lung problems.
● a bowel blockage or have narrowing of the stomach or intestines.
● known hypersensitivity to hydrocodone or acetaminophen, or any ingredient in Hydrocodone Bitartrate and Acetaminophen Tablets.

Before taking Hydrocodone Bitartrate and Acetaminophen Tablets, tell your healthcare provider if you have a history of:

● head injury, seizures

● problems urinating

● liver, kidney, thyroid problems

● pancreas or gallbladder problems

● abuse of street or prescription drugs, alcohol addiction, opioid overdose, or mental health problems

● Tell your healthcare provider if you are:
● noticing your pain getting worse. If your pain gets worse after you take Hydrocodone Bitartrate and Acetaminophen tablets, do not take more of Hydrocodone Bitartrate and Acetaminophen tablets without first talking to your healthcare provider. Talk to your healthcare provider if the pain that you have increases, if you feel more sensitive to pain, or if you have new pain after taking Hydrocodone Bitartrate and Acetaminophen tablets.
● Are pregnant or planning to become pregnant . Use of Hydrocodone Bitartrate and Acetaminophen Tablets for an extended period of time during pregnancy can cause withdrawal symptoms in your newborn baby that could be life-threatening if not recognized and treated.
● breastfeeding. Hydrocodone bitartrate and acetaminophen passes into breast milk and may harm your baby. Carefully observe infants for increased sleepiness (more than usual), breathing difficulties, or limpness. Seek immediate medical care if you notice these signs.
● living in a household where there are small children or someone who has abused street or prescription drugs
● taking prescription or over-the-counter medicines, vitamins, or herbal supplements. Taking Hydrocodone Bitartrate and Acetaminophen Tablets with certain other medicines can cause serious side effects that could lead to death.

When taking Hydrocodone Bitartrate and Acetaminophen Tablets:
● Do not change your dose. Take Hydrocodone Bitartrate and Acetaminophen tablets exactly as prescribed by your healthcare provider. Use the lowest dose possible for the shortest time needed.
● For acute (short-term) pain, you may only need to take Hydrocodone Bitartrate and Acetaminophen tablets for a few days. You may have some Hydrocodone Bitartrate and Acetaminophen tablets left over that you did not use. See disposal information at the bottom of this section for directions on how to safely throw away (dispose of) your unused Hydrocodone Bitartrate and Acetaminophen tablets.
● Take your prescribed dose every four to six hours as needed for pain.
● Do not take more than your prescribed dose. If you miss a dose, take your next dose at your usual time.
● Call your healthcare provider if the dose you are taking does not control your pain.
● If you have been taking Hydrocodone Bitartrate and Acetaminophen Tablets regularly, do not stop taking Hydrocodone Bitartrate and Acetaminophen Tablets without talking to your healthcare provider.
● Dispose of expired, unwanted, or unused Hydrocodone Bitartrate and Acetaminophen Tablets by promptly flushing down the toilet, if a drug take-back option is not readily available. Visit www.fda.gov/drugdisposal for additional information on disposal of unused medicines.

While taking Hydrocodone Bitartrate and Acetaminophen Tablets DO NOT:
● Drive or operate heavy machinery, until you know how Hydrocodone Bitartrate and Acetaminophen Tablets affects you. Hydrocodone Bitartrate and Acetaminophen Tablets can make you sleepy, dizzy, or lightheaded.
● Drink alcohol or use prescription or over-the-counter medicines that contain alcohol. Using products containing alcohol during treatment with Hydrocodone Bitartrate and Acetaminophen Tablets may cause you to overdose and die.

The possible side effects of Hydrocodone Bitartrate and Acetaminophen Tablets:
● constipation, nausea, sleepiness, vomiting, tiredness, headache, dizziness, abdominal pain. Call your healthcare provider if you have any of these symptoms and they are severe.
Get emergency medical help or call 911 right away if you have:
● trouble breathing, shortness of breath, fast heartbeat, chest pain, swelling of your face, tongue, or throat, extreme drowsiness, light-headedness when changing positions, feeling faint, agitation, high body temperature, trouble walking, stiff muscles, or mental changes such as confusion.
These are not all the possible side effects of Hydrocodone Bitartrate and Acetaminophen Tablets. Call your healthcare provider for medical advice about side effects. You may report side effects to FDA at 1-800-FDA-1088. For more information, contact Strides Pharma Inc at 1-877-244-9825
Distributed by:
Strides Pharma Inc.
Bridgewater, NJ 08807
Revised: 01/2026

This Medication Guide has been approved by the U.S. Food and Drug Administration.